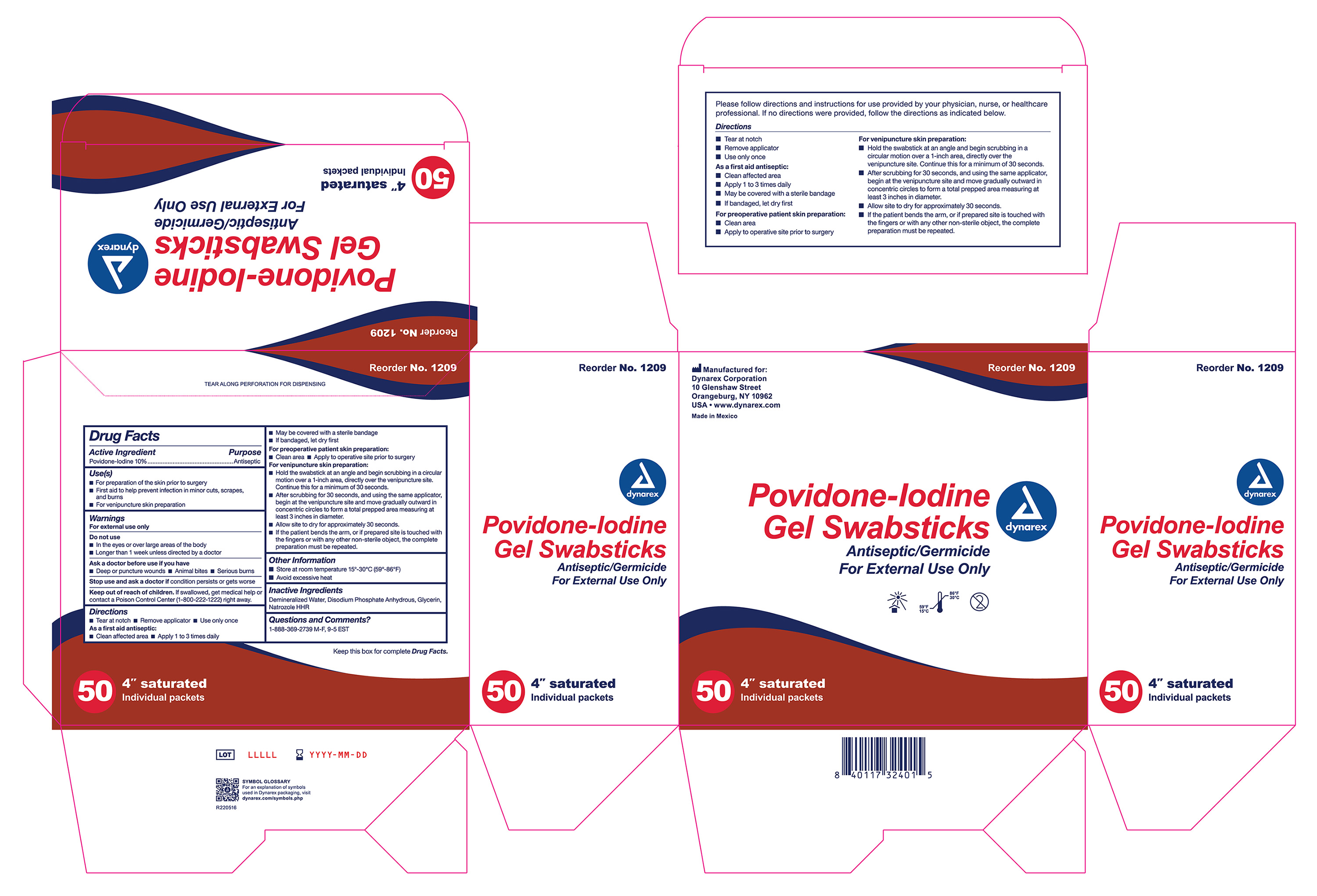 DRUG LABEL: Povidone Iodine Gel Swabstick
NDC: 67777-418 | Form: GEL
Manufacturer: Dynarex Corporation
Category: otc | Type: HUMAN OTC DRUG LABEL
Date: 20240213

ACTIVE INGREDIENTS: POVIDONE-IODINE 10 mg/1 mL
INACTIVE INGREDIENTS: GLYCERIN; HYDROXYETHYL CELLULOSE (4000 MPA.S AT 1%); SODIUM PHOSPHATE, DIBASIC, ANHYDROUS; WATER

Povidone Iodine Gel Swabstick NDC 67777-418

Active Ingredient

Povidone-Iodine 10%

Purpose

Antiseptic

Use(s)

• For preparation of the skin prior to surgery

• First aid to help prevent infection in minor cuts, scrapes, and burns

• For venipuncture skin preparation

Warnings

For External Use Only

Do not use

• In the eyes or over large areas of the body

• Longer than 1 week unless directed by a doctor

Ask a doctor before use if you have

• Deep or puncture wounds

• Animal bites

• Serious burns

Stop use and ask a doctor if

Condition persists or gets worse

Keep out of reach of children

If swallowed, get medical help or contact a Poison Control Center (800-222-1222) right away.

Directions

• Tear at notch • Remove applicator • Use only once

As a first aid antiseptic:

• Clean affected area

• Apply 1 to 3 times daily

• May be covered with a sterile bandage

• If bandaged, let dry first

For preoperative patient skin preparation:

• Clean area

• Apply to operative site prior to surgery

For Venipuncture skin preparation:

• Hold the swabstick at an angle and begin scrubbing in a circular motion over a 1-inch area, directly over the venipuncture site. Continue this for a minimum of 30 seconds.

• After scrubbing for 30 seconds, and using the same applicator, begin at the venipuncture site and move gradually outward in concentric circles to form a total prepped area measuring at least 3 inches in diameter.

• Allow site to dry for approximately 30 seconds.

• If the patient bend the arm, or if prepared site is touched with the fingers or with any other non-sterile object, the complete preparation must be repeated.

Other Information

• Store at room temperature 15º-30ºC (59º-86ºF)

• Avoid excessive heat

Inactive Ingredients

Demineralized Water, Disodium Phosphate Anhydrous, Glycerin, Natrozole HHR

Questions and Comments?

1-888-369-2739 M-F, 9-5 EST

Label

1209 Povidone-Iodine Gel Swabstick